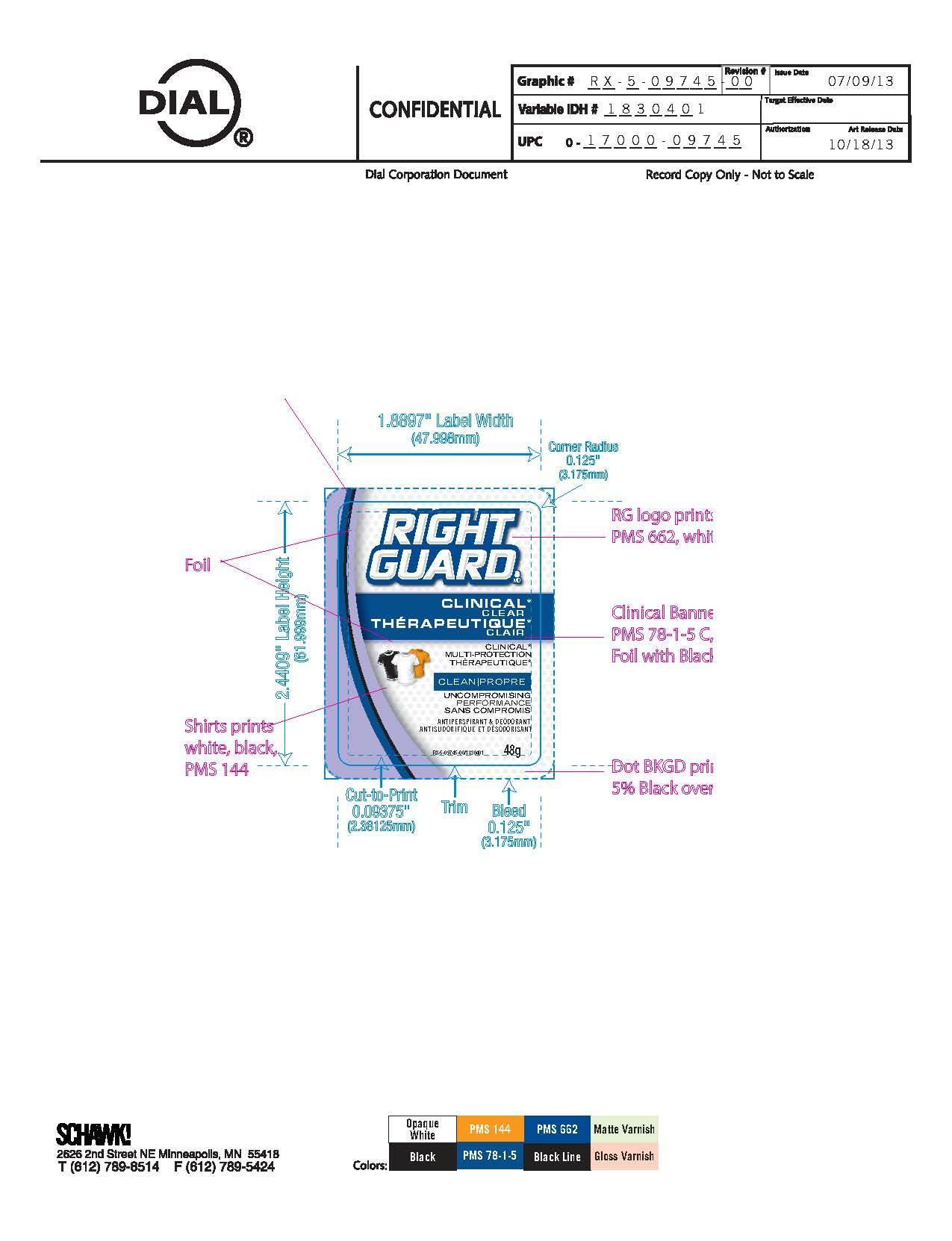 DRUG LABEL: Right Guard Clinical Clear
NDC: 51815-216 | Form: STICK
Manufacturer: VVF Illinois Services
Category: otc | Type: HUMAN OTC DRUG LABEL
Date: 20140227

ACTIVE INGREDIENTS: ALUMINUM ZIRCONIUM TETRACHLOROHYDREX GLY 48 g/48 g
INACTIVE INGREDIENTS: WATER; HIGH DENSITY POLYETHYLENE; DODECAMETHYLPENTASILOXANE; C12-15 ALKYL BENZOATE; PROPYLENE GLYCOL; CETYL PEG/PPG-10/1 DIMETHICONE (HLB 2); PEG/PPG-14/4 DIMETHICONE; SYNTHETIC WAX (1200 MW)

Right Guard Clinical Clear

Active Ingredient

Aluminum Zirconium Tetrachlorohydrex GLY 20.0%

Purpose

Antiperspirant

Warnings

For external use only
Do not use on broken skin

Stop use and ask a doctor if rash or irritation occurs

Keep out of reach of children.

If swallowed, get medical help or contact a poison control center right away

Use

Reduces underarm perspiration

Ask a doctor before use if you have kidney disease

Inactive Ingredients

Water, Polyethylene,

cyclohexasiloxane, C12-15 alkyl benzoate,

propylene glycol, fragrance, cetyl PEG/PPG-10/1

dimethicone, Bis-PEG/PPG-14/14

dimethicone/dimethicone, synthetic wax.

Questions?

1-800-258-DIAL

Directions

Apply to underarms only